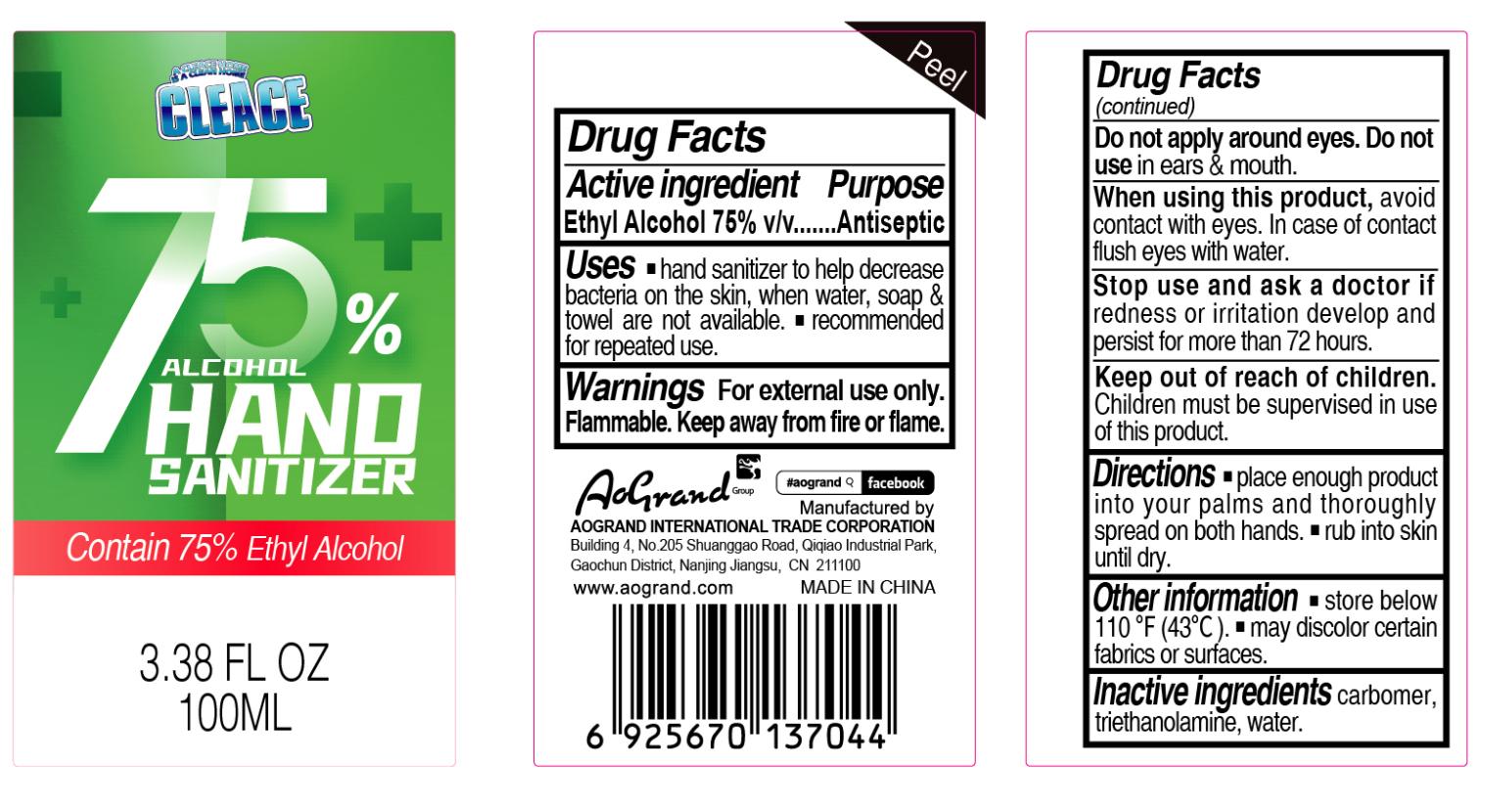 DRUG LABEL: Cleace 75% Alcohol Hand Sanitizer
NDC: 74621-029 | Form: GEL
Manufacturer: Aogrand International Trade Corporation
Category: otc | Type: HUMAN OTC DRUG LABEL
Date: 20230211

ACTIVE INGREDIENTS: ALCOHOL 75 mL/100 mL
INACTIVE INGREDIENTS: CARBOMER HOMOPOLYMER, UNSPECIFIED TYPE; WATER; TROLAMINE

Cleace 75% Alcohol Hand Sanitizer

Active Ingredient

Ethyl Alcohol 75% v/v Antiseptic

Purpose

Antiseptic, Hand Sanitizer

Uses

- hand sanitizer to help decrease bacteria on the skin, when water, soap & towel are not available.
- recommended for repeated use.

Warnings

For external use only. Flammable.

Keep away from fire or flame.

When using this product

avoid contact with eyes. In case of contact flush eyes with water.

Stop use and ask a doctor

if redness or irritation develop and persist for more than 72 hours.

Keep out of reach of children.

Children must be surpervised in use of this product.

Directions

- Place enough product into your palms and thoroughly spread on both hands.
- Rub into skin until dry.

Other information

- store below 110F (43C)
- may discolor certain fabrics or surfaces.

Inactive ingredients

carbomer, triethanolamine, water

Package Label - Principal Display Panel

100mL NDC: 74621-029-01

A CLEACE HOME

IS A CLEAN HOME

CLEACE

75%

ALCOHOL HAND SANITIZER

Contain 75% Ethyl Alcohol

3.38 FL OZ (100mL)